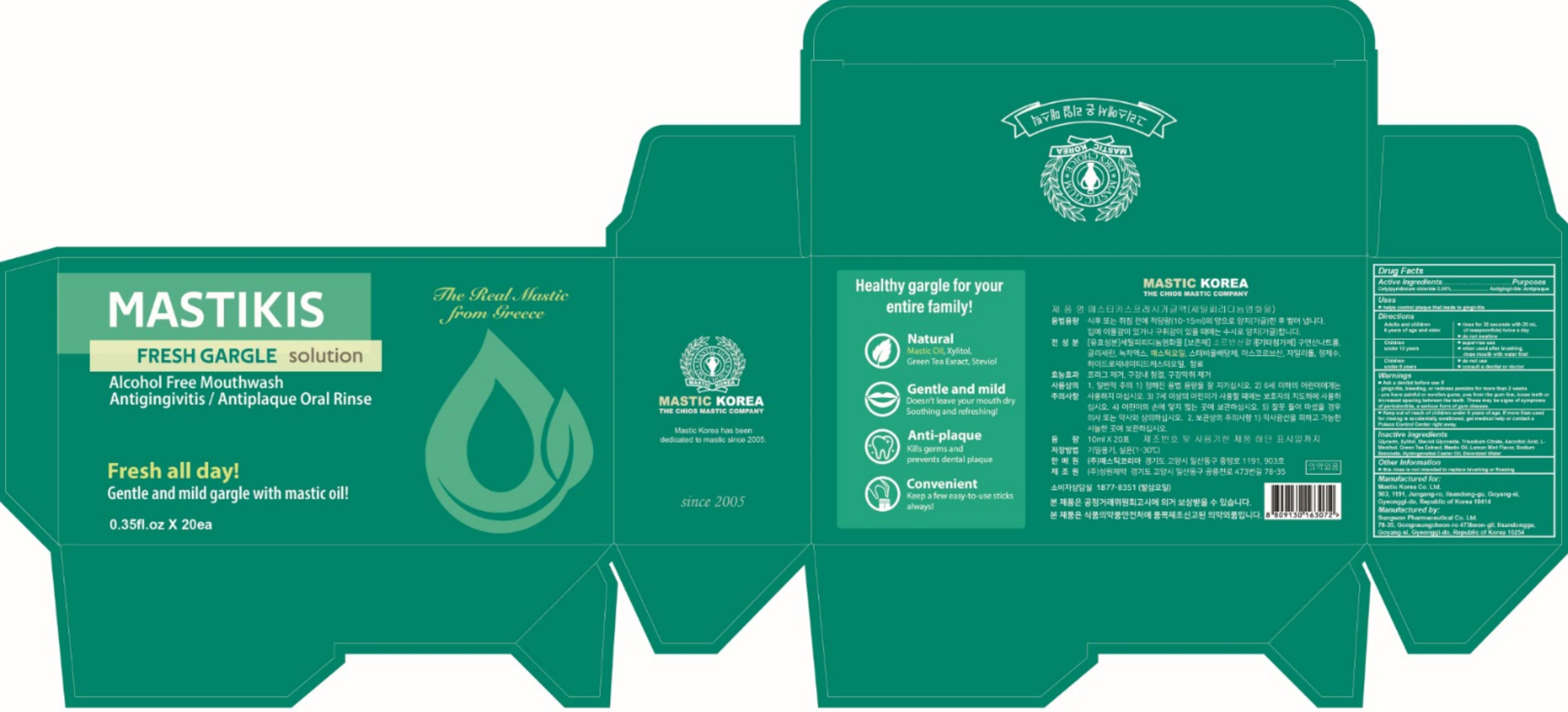 DRUG LABEL: Mastikis fresh gargle
NDC: 79814-007 | Form: MOUTHWASH
Manufacturer: Mastic Korea.Co.Ltd
Category: otc | Type: HUMAN OTC DRUG LABEL
Date: 20200921

ACTIVE INGREDIENTS: CETYLPYRIDINIUM CHLORIDE 0.5 mg/1 mL
INACTIVE INGREDIENTS: WATER; GLYCERIN; XYLITOL; STEVIOSIDE; SODIUM CITRATE, UNSPECIFIED FORM; ASCORBIC ACID; LEVOMENTHOL; GREEN TEA LEAF; SODIUM BENZOATE; HYDROGENATED CASTOR OIL

79814-007_Mastikis fresh gargle

Active ingredient

Cetylpyridinium chloride 0.05%

Purpose

Antigingivitis, Antiplaque

Use

helps control plaque that leads to gingivitis

Warnings

Ask a dentist before use if
- gingivitis, bleeding, or redness persists for more than 2 weeks
- you have painful or swollen gums, pus from the gum line, loose teeth or increased spacing between the teeth. These may be signs of symptoms of periodontitis, a serious form of gum disease.

Stop use and ask a dentist if

- gingivitis, bleeding, or redness persists for more than 2 weeks
- you have painful or swollen gums, pus from the gum line, loose teeth or increased spacing between the teeth. These may be signs of symptoms of periodontitis, a serious form of gum disease.

Keep out of reach of children under 6 years of age

If more than used for rinsing is accidentally swallowed, get medical help or contact a Poison Control Center right away.

Directions

- adults and children 6 years & older: rinse for 30 seconds with 20 mL (4 teaspoonfuls) twice a day
- do not swallow
- children 6 years to under 12 years of age: supervise use
- when used after brushing, rinse mouth with water first
- children under 6 years of age: do not use consult a dentist or doctor

Other information

- this rinse is not intended to replace brushing or flossing

Inactive ingredients

Glycerin, Xylitol, Steviol Glycoside, Trisodium Citrate, Ascorbic Acid, L-Menthol, Green Tea Extract, Mastic Oil, Lemon Mint Flavor, Sodium Benzoate, Hydrogenated Caster Oil, Deionized Water